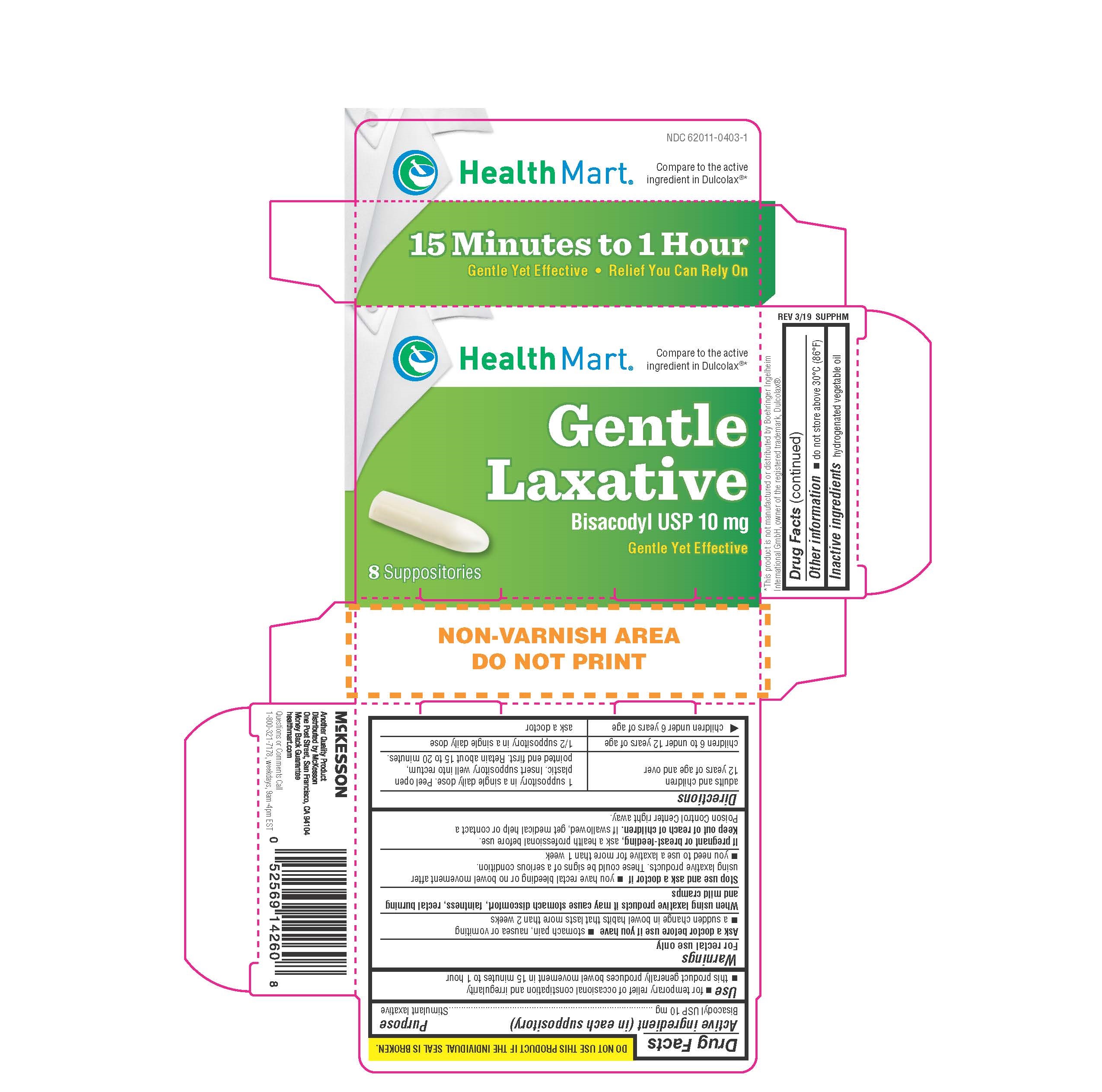 DRUG LABEL: Foster and Thrive Gentle Laxative
NDC: 70677-1091 | Form: SUPPOSITORY
Manufacturer: Strategic Sourcing Services LLC
Category: otc | Type: HUMAN OTC DRUG LABEL
Date: 20241218

ACTIVE INGREDIENTS: BISACODYL 10 mg/2000 mg
INACTIVE INGREDIENTS: FAT, HARD

DRUG FACTS

Active ingredient

Bisacodyl USP, 10 mg

Purpose

Stimulant Laxative

Uses

- For relief of occasional constipation and irregularity
- -This product generally produces bowel movement in 15 minutes to 1 hour

Warnings

For rectal use only.

ASK DOCTOR

- stomach pain, nausea or vomiting
- noticed a sudden change in bowel habits that persists over a period of two weeks

When using this product

May cause abdominal discomfort, faintness, rectal burning, and mild cramps

Stop use and ask a doctor if

- if you have rectal bleeding or fail to have bowel movement after using a laxative. This may indicate a serious condition
- you need to use a laxative for more than 1 week

PREGNANCY OR BREAST FEEDING

If pregnant or breast-feeding, ask a health professional before use.

Keep out of reach of children

If swallowed, get medical help or contact a Poison Control Center right away.

Directions

Adults and children 12 years of age and older Children 6 to under 12 years Children under 6

One suppository once daily 1/2 suppository once daily Ask doctor.

-Detach one suppository from the strip and remove from foil - Carefully insert one suppositry well into the rectum

-Do not use more than once per day

Other Information

- do not store above 30°C (86°F)

Inactive Ingredients

hydrogenated vegetable oil